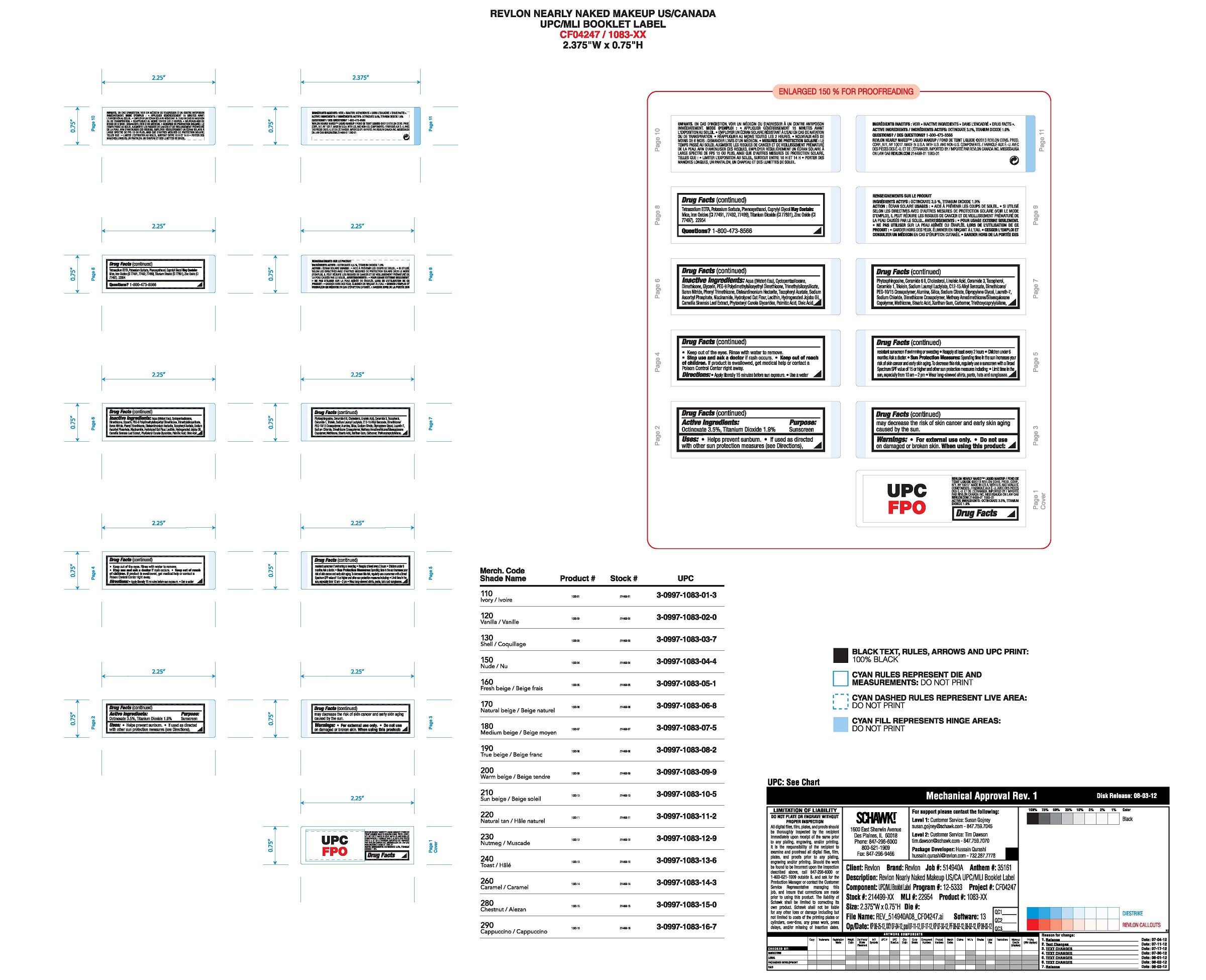 DRUG LABEL: Revlon Nearly Naked Makeup
NDC: 10967-622 | Form: LIQUID
Manufacturer: Revlon Consumer Products Corp
Category: otc | Type: HUMAN OTC DRUG LABEL
Date: 20161129

ACTIVE INGREDIENTS: OCTINOXATE 3.5 mg/1 mL; TITANIUM DIOXIDE 1.9 mg/1 mL
INACTIVE INGREDIENTS: WATER; DIMETHICONE; PHENYL TRIMETHICONE; METHICONE (20 CST); LAURETH-7; ALUMINUM OXIDE; .ALPHA.-TOCOPHEROL ACETATE; XANTHAN GUM; NIACINAMIDE; SODIUM LAUROYL LACTYLATE; CERAMIDE 6 II; CERAMIDE 1; PHYTOSPHINGOSINE; CHOLESTEROL; TRIMETHYLSILOXYSILICATE (M/Q 0.8-1.0); CYCLOMETHICONE 5; PEG-9 POLYDIMETHYLSILOXYETHYL DIMETHICONE; BORON NITRIDE; DISTEARDIMONIUM HECTORITE; PHENOXYETHANOL; SODIUM CHLORIDE; POTASSIUM SORBATE; TRIETHOXYCAPRYLYLSILANE; SODIUM ASCORBYL PHOSPHATE; SODIUM CITRATE; DIPROPYLENE GLYCOL; TOCOPHEROL; LINOLEIC ACID; LECITHIN, SOYBEAN; PALMITIC ACID; OLEIC ACID; STEARIC ACID; SILICON DIOXIDE; OATMEAL; EDETATE SODIUM; ALKYL (C12-15) BENZOATE; GREEN TEA LEAF; GLYCERYL TRIOLEATE; HYDROGENATED JOJOBA OIL; CARBOXYPOLYMETHYLENE

Revlon Nearly Naked Makeup

Active Ingredients:

Octinoxate: 3.5%

Titanium Dioxide 9.5%

Purpose

Sunscreen

Uses:

•Helps prevent sunburn
•If used as directed with other sun protection measures (see Directions), decreases the risk of skin cancer and early skin aging caused by the sun

Warnings:

•For external use only
•Do notuse on damaged or broken skin
•When using this product: Keep out of eyes. Rinse with water to remove.
•Stop use and ask a doctor if a rash occurs
•Keep out of reach of children. If product is swallowed, get medical help or contact a Poison Control center right away

Directions

•Apply liberally 15 minutes before sun exposure
•Use a water resistant sunscreen if swimming or sweating
•Reapply at least every 2 hours
•Children under 6 months: Ask a doctor.

Sun Protection Measures

Spending time in the sun increases your risk of skin cancer and early skin aging. To decrease this risk, regularly use a sunscreen with a Broad Spectrum SPF value of 15 or higher and other sun protection measures including:
•Limit time in the sun, especially from 10 am - 2 pm
•Wear long-sleeved shirts, pants, hats and sunglasses.

Inactive Ingredients

AQUA ((WATER) EAU), CYCLOPENTASILOXANE, DIMETHICONE, GLYCERIN, PEG-9 POLYDIMETHYLSILOXYETHYL DIMETHICONE, TRIMETHYLSILOXYSILICATE, PHENYL TRIMETHICONE, BORON NITRIDE, DISTEARDIMONIUM HECTORITE, DIMETHICONE/PEG-10/15 CROSSPOLYMER, ALUMINA, SILICA, CAPRYLYL GLYCOL, PHENOXYETHANOL, LAURETH-7, SODIUM CHLORIDE, DIMETHICONE CROSSPOLYMER, METHICONE, XANTHAN GUM, POTASSIUM SORBATE, TRIETHOXYCAPRYLYLSILANE, SODIUM ASCORBYL PHOSPHATE, NIACINAMIDE, HYDROLYZED OAT FLOUR, TETRASODIUM EDTA, TOCOPHERYL ACETATE, C12-15 ALKYL BENZOATE, TOCOPHEROL, SODIUM CITRATE, DIPROPYLENE GLYCOL, SODIUM LAUROYL LACTYLATE, CAMELLIA SINENSIS LEAF EXTRACT, LINOLEIC ACID, LECITHIN, METHOXY AMODIMETHICONE/SILSESQUIOXANE COPOLYMER, PHYTOSTERYL CANOLA GLYCERIDES, PALMITIC ACID, OLEIC ACID, CERAMIDE 3, STEARIC ACID, TRIOLEIN, HYDROGENATED JOJOBA OIL, PHYTOSPHINGOSINE, CERAMIDE 6 II, CHOLESTEROL, CARBOMER, CERAMIDE 1

Principal Display Panel

REVLON

Nearly Naked Makeup

Broad Spectrum

SPF 20

1.0 fL. OZ/30 mL